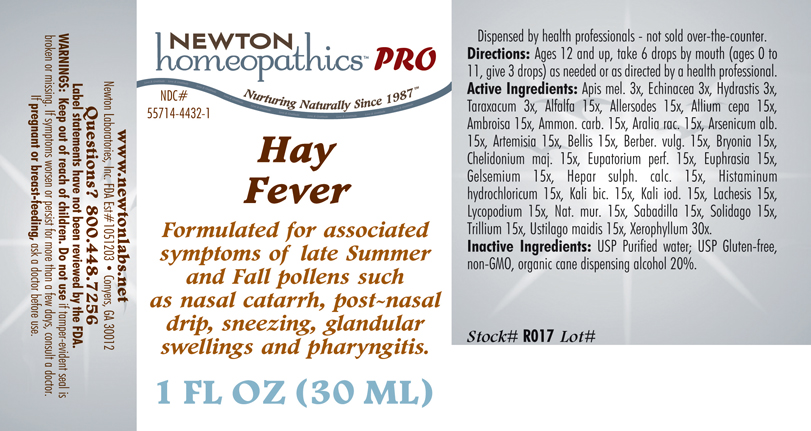 DRUG LABEL: Hay Fever 
NDC: 55714-4432 | Form: LIQUID
Manufacturer: Newton Laboratories, Inc.
Category: homeopathic | Type: HUMAN PRESCRIPTION DRUG LABEL
Date: 20110601

ACTIVE INGREDIENTS: Xerophyllum Asphodeloides 30 [hp_X]/1 mL; Alfalfa 15 [hp_X]/1 mL; Avena Sativa Pollen 15 [hp_X]/1 mL; Cynosurus Cristatus Pollen 15 [hp_X]/1 mL; Echinochloa Crus-galli Pollen 15 [hp_X]/1 mL; Poa Pratensis Pollen 15 [hp_X]/1 mL; Anthoxanthum Odoratum Pollen 15 [hp_X]/1 mL; Agrostis Gigantea Pollen 15 [hp_X]/1 mL; Bromus Secalinus Pollen 15 [hp_X]/1 mL; Alopecurus Pratensis Pollen 15 [hp_X]/1 mL; Phleum Pratense Pollen 15 [hp_X]/1 mL; Festuca Pratensis Pollen 15 [hp_X]/1 mL; Holcus Lanatus Pollen 15 [hp_X]/1 mL; Lolium Perenne Pollen 15 [hp_X]/1 mL; Fagus Sylvatica Pollen 15 [hp_X]/1 mL; Betula Pendula Pollen 15 [hp_X]/1 mL; Quercus Alba Pollen 15 [hp_X]/1 mL; Fraxinus Excelsior Pollen 15 [hp_X]/1 mL; Corylus Americana Pollen 15 [hp_X]/1 mL; Populus Nigra Pollen 15 [hp_X]/1 mL; Platanus Orientalis Pollen 15 [hp_X]/1 mL; Ulmus Glabra Pollen 15 [hp_X]/1 mL; Salix Alba Pollen 15 [hp_X]/1 mL; Narcissus Pseudonarcissus 15 [hp_X]/1 mL; Rosa Canina Flower 15 [hp_X]/1 mL; Lilium Candidum Flower 15 [hp_X]/1 mL; Primula Vulgaris 15 [hp_X]/1 mL; Dianthus Caryophyllus Flower 15 [hp_X]/1 mL; Ulex Europaeus Flower 15 [hp_X]/1 mL; Cytisus Scoparius Pollen 15 [hp_X]/1 mL; Calluna Vulgaris Pollen 15 [hp_X]/1 mL; Crataegus Monogyna Pollen 15 [hp_X]/1 mL; Aconitum Napellus 15 [hp_X]/1 mL; Arundo Pliniana Root 15 [hp_X]/1 mL; Dysphania Ambrosioides 15 [hp_X]/1 mL; Helianthemum Canadense 15 [hp_X]/1 mL; Drosera Rotundifolia 15 [hp_X]/1 mL; Solanum Dulcamara Top 15 [hp_X]/1 mL; Ledum Palustre Twig 15 [hp_X]/1 mL; Onosmodium Virginianum Whole 15 [hp_X]/1 mL; Populus Tremuloides Leaf 15 [hp_X]/1 mL; Populus Tremuloides Bark 15 [hp_X]/1 mL; Pulsatilla Vulgaris 15 [hp_X]/1 mL; Sanguinaria Canadensis Root 15 [hp_X]/1 mL; Datura Stramonium 15 [hp_X]/1 mL; Elymus Repens Root 15 [hp_X]/1 mL; Urtica Urens 15 [hp_X]/1 mL; Wyethia Helenioides Root 15 [hp_X]/1 mL; Onion 15 [hp_X]/1 mL; Ambrosia Artemisiifolia 15 [hp_X]/1 mL; Ammonium Carbonate 15 [hp_X]/1 mL; Aralia Racemosa Root 15 [hp_X]/1 mL; Arsenic Trioxide 15 [hp_X]/1 mL; Artemisia Vulgaris Root 15 [hp_X]/1 mL; Bellis Perennis 15 [hp_X]/1 mL; Berberis Vulgaris Root Bark 15 [hp_X]/1 mL; Bryonia Alba Root 15 [hp_X]/1 mL; Chelidonium Majus 15 [hp_X]/1 mL; Eupatorium Perfoliatum Flowering Top 15 [hp_X]/1 mL; Euphrasia Stricta 15 [hp_X]/1 mL; Gelsemium Sempervirens Root 15 [hp_X]/1 mL; Calcium Sulfide 15 [hp_X]/1 mL; Histamine Dihydrochloride 15 [hp_X]/1 mL; Potassium Dichromate 15 [hp_X]/1 mL; Potassium Iodide 15 [hp_X]/1 mL; Lachesis Muta Venom 15 [hp_X]/1 mL; Lycopodium Clavatum Spore 15 [hp_X]/1 mL; Sodium Chloride 15 [hp_X]/1 mL; Schoenocaulon Officinale Seed 15 [hp_X]/1 mL; Solidago Virgaurea Flowering Top 15 [hp_X]/1 mL; Trillium Erectum Root 15 [hp_X]/1 mL; Ustilago Maydis 15 [hp_X]/1 mL; Apis Mellifera 3 [hp_X]/1 mL; Echinacea, Unspecified 3 [hp_X]/1 mL; Goldenseal 3 [hp_X]/1 mL; Taraxacum Officinale 3 [hp_X]/1 mL
INACTIVE INGREDIENTS: Alcohol; Water

Hay Fever

INDICATIONS & USAGE SECTION

Formulated for associated symptoms of late Summer and Fall pollens such as nasal catarrh, post-nasal drip, sneezing, glandular swelling and pharyngitis.

DOSAGE & ADMINISTRATION SECTION

Directions: Ages 12 and up, take 6 drops by mouth (ages 0 to 11, give 3 drops) as needed or as directed by a health professional.

OTC - ACTIVE INGREDIENT SECTION

Xerophyllum 30x, Alfalfa 15x, Allersodes 15x, Allium cepa 15x, Ambrosia 15x, Ammon. carb. 15x, Aralia rac. 15x, Arsenicum alb. 15x, Artemisia 15x, Bellis 15x, Berber. vulg. 15x, Bryonia 15x , Chelidonium maj. 15x, Eupatorium perf. 15x, Euphrasia 15x, Gelsemium 15x, Hepar sulph. calc. 15x, Histaminum hydrochloricum 15x, Kali bic. 15x, Kali iod. 15x, Lachesis 15x, Lycopodium 15x, Nat.mur. 15x, Sabadilla 15x, Solidago 15x, Trillium 15x, Ustilago maidis 15x, Apis mel. 3x, Echinacea 3x, Hydrastis 3x, Taraxacum 3x.

OTC - PURPOSE SECTION

Formulated for associated symptoms of late Summer and Fall pollens such as nasal catarrh, post-nasal drip, sneezing, glandular swelling and pharyngitis.

INACTIVE INGREDIENT SECTION

Inactive Ingredients: USP Purified Water; USP Gluten-free, non-GMO, organic cane dispensing alcohol 20%.

QUESTIONS SECTION

www.newtonlabs.net Newton Laboratories, Inc. FDA Est # 1051203 - Conyers, GA 30012
Questions? 1.800.448.7256

WARNINGS SECTION

Warning: Keep out of reach of children. Do not use if tamper-evident seal is broken or missing. If symptoms worsen or persist for more than a few days, consult a doctor. If pregnant or breast-feeding, ask a doctor before use.

OTC - PREGNANCY OR BREAST FEEDING SECTION

If pregnant or breast-feeding, ask a doctor before use.

OTC - KEEP OUT OF REACH OF CHILDREN SECTION

Keep out of reach of children.